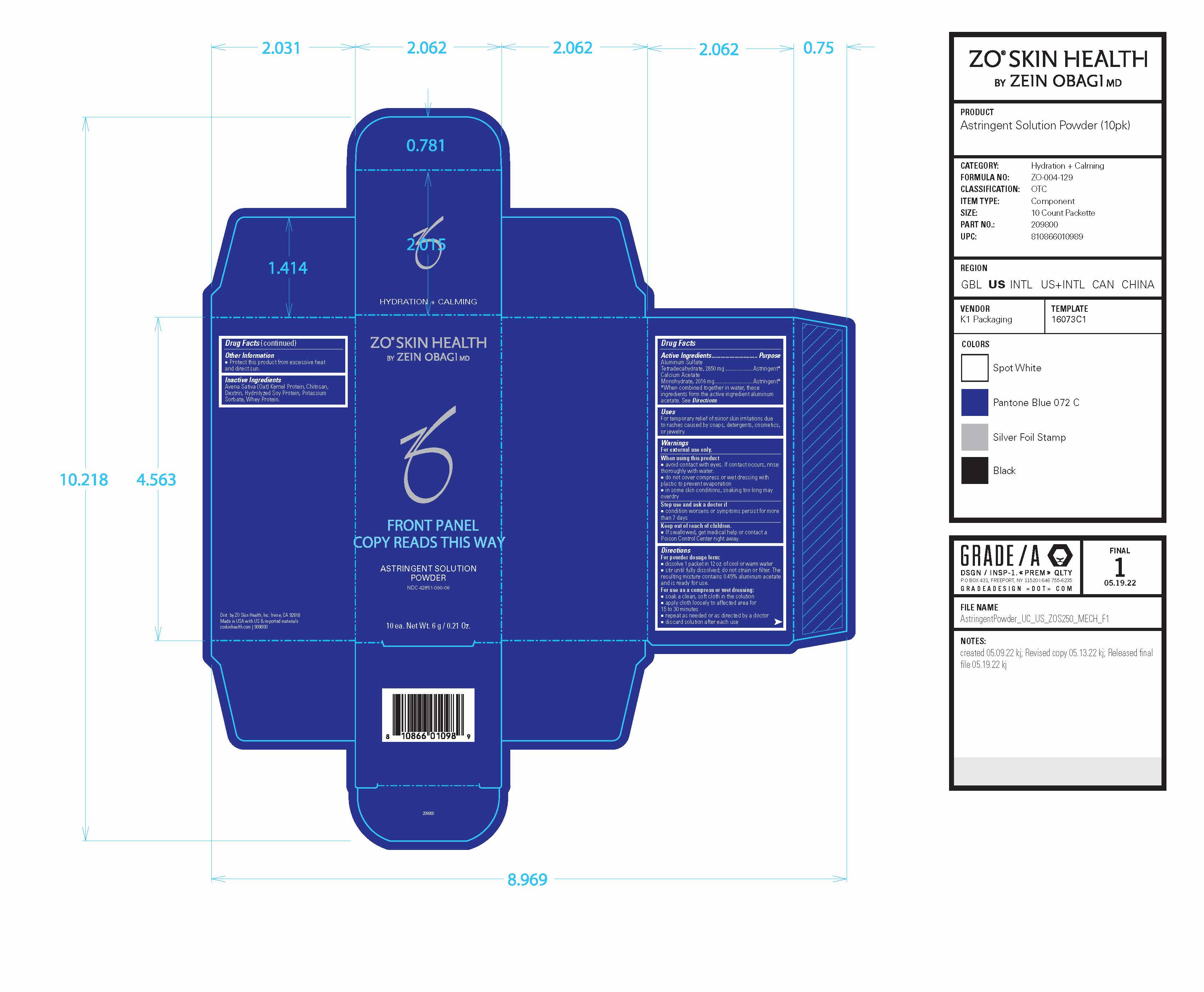 DRUG LABEL: ZO Skin Health Astringent Solution
NDC: 42851-090 | Form: POWDER
Manufacturer: ZO Skin Health, Inc.
Category: otc | Type: HUMAN OTC DRUG LABEL
Date: 20241031

ACTIVE INGREDIENTS: ALUMINUM ACETATE 4866 mg/6 g
INACTIVE INGREDIENTS: WHEY; POTASSIUM SORBATE; HYDROLYZED SOY PROTEIN (ENZYMATIC; 2000 MW)

ZO® Skin Health Astringent Solution Powder
National Drug Code 42851-090-06

Drug Facts

Active Ingredients | Purpose
Aluminum Sulfate Tetradecahydrate, 2850 mg | Astringent*
Calcium AcetateMonohydrate, 2016 mg | Astringent*

*When combined together in water, these ingredients form the active ingredient aluminum acetate. See Directions

Uses

For temporary relief of minor skin irritations due to rashes caused by soaps, detergents, cosmetics, or jewelry.

Warnings

For external use only.

When using this product

■ avoid contact with eyes. If contact occurs, rinse thoroughly with water.

■ do not cover compress or wet dressing with plastic to prevent evaporation

■ in some skin conditions, soaking too long may overdry

Stop use and ask a doctor

■ if condition worsens or symptoms persist for more than 7 days

Keep out of reach of children.

■ if swallowed, get medical help or contact a Poison Control Center right away.

Directions

For powder dosage form:

■ dissolve 1 packet in 12 oz. of cool or warm water
■ stir until fully dissolved; do not strain or filter. The resulting mixture contains 0.45% aluminum acetate and is ready for use.
For use as a compress or wet dressing:
■ soak a clean, soft cloth in the solution
■ apply cloth loosely to affected area for
15 to 30 minutes
■ repeat as needed or as directed by a doctor
■ discard solution after each use

Other Information

■ Protect this product from excessive heat and direct sun

Inactive Ingredients

Avena Sativa (Oat) Kernel Protein, Chitosan, Dextrin, Hydrolyzed Soy Protein, Potassium Sorbate, Whey Protein.

RECENT MAJOR CHANGES

- Added bolded subheadings within Directions section.